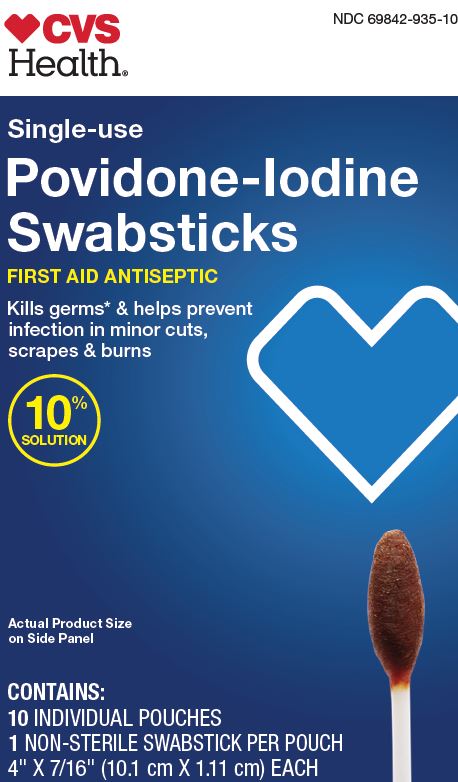 DRUG LABEL: CVS Povidone Iodine
NDC: 69842-935 | Form: SWAB
Manufacturer: CVS Pharmacy Inc
Category: otc | Type: HUMAN OTC DRUG LABEL
Date: 20250103

ACTIVE INGREDIENTS: POVIDONE-IODINE 10 mg/1 mL
INACTIVE INGREDIENTS: CITRIC ACID MONOHYDRATE; WATER; SODIUM PHOSPHATE, DIBASIC, ANHYDROUS

69842-935 CVS PVP Swabsticks

Active Ingredient

Povidone-Iodine 10% w/v

Purpose

First aid antiseptic

Uses

- • first aid antiseptic to help prevent infection in minor cuts, scrapes and burns

Warnings

For external use only.

Do not use

- • in the eyes
- • longer than one week unless directed by a physician
- • on individuals who are allergic or sensitive to iodine
- • over large areas of the body

Stop use and ask a doctor

- • irritation and redness develop
- • condition persists for more than 72 hours
- • in case of deep or puncture wounds, animal bites or serious burns

Keep out of reach of children.

If swallowed, seek medical assistance or immediately contact a Poison Control Center.

Directions

- • clean the affected area
- • apply a small amount of this product on the area 1-3 times daily
- • may be covered with a sterile bandage
- • if bandaged, let dry first

Other information

- • protect from freezing and avoid excessive heat

Inactive ingredients

citric acid, disodium phosphate, purified water

Manufacturing Information

Distributed by:

CVS Pharmacy, Inc.

One CVS Drive, Woonsocket, RI 02895 USA

Made in China

www.CVS.com

1-800-SHOP CVS

REF: CVS239100

V2 RK21LPD